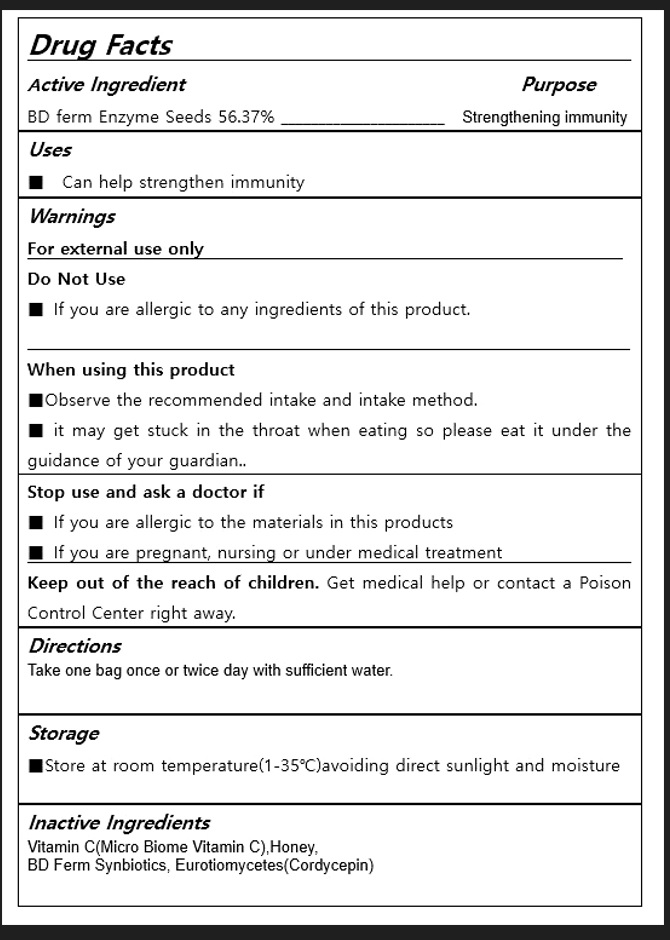 DRUG LABEL: BD FERM CORDYCEPIN BIOME C2000
NDC: 82332-120 | Form: POWDER
Manufacturer: BDFERM BIOTECH CO,.LTD
Category: otc | Type: HUMAN OTC DRUG LABEL
Date: 20240307

ACTIVE INGREDIENTS: HYDROLYZED WHEAT PROTEIN (ENZYMATIC, 3000 MW) 56.37 g/100 g
INACTIVE INGREDIENTS: SACCHAROMYCES CEREVISIAE; CORDYCEPIN; BIFIDOBACTERIUM ANIMALIS LACTIS; ASCORBIC ACID; HONEY

inactive ingredints

Vitamin C(Micro Biome Vitamin C)36%,
Honey,
BD Ferm Synbiotics,
Eurotiomycetes(Cordycepin)

Direction

Take one bag once or twice day with sufficient water.

Keep out of reach of children

Keep out of the reach of children. Get medical help or contact a Poison Control Center right away.

Stop use and ask a doctor if

■ If you are allergic to the materials in this products

■ If you are pregnant, nursing or under medical treatment

PURPOSE

Strengthening immunity

Uses

Helps recover from fatigue, stimulate your digestion, and enhance your immune system. Our proprietary technology is what makes its creation possible.

ACTIVE INGREDIENT

BD ferm Enzyme Seeds

DO NOT USE

If you are allergic to any ingredients of this product.

WHEN USING

■Observe the recommended intake and intake method.

■ it may get stuck in the throat when eating so please eat it under the guidance of your guardian..

WARNINGS

For external use only

PACKAGE LABEL

bd ferm